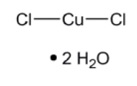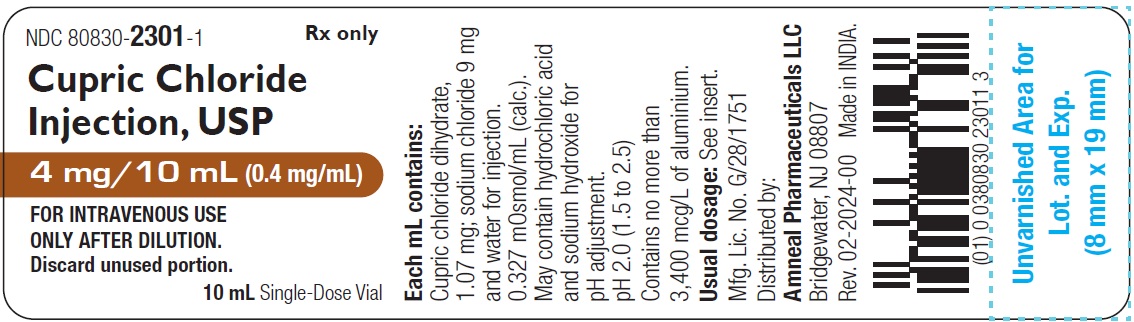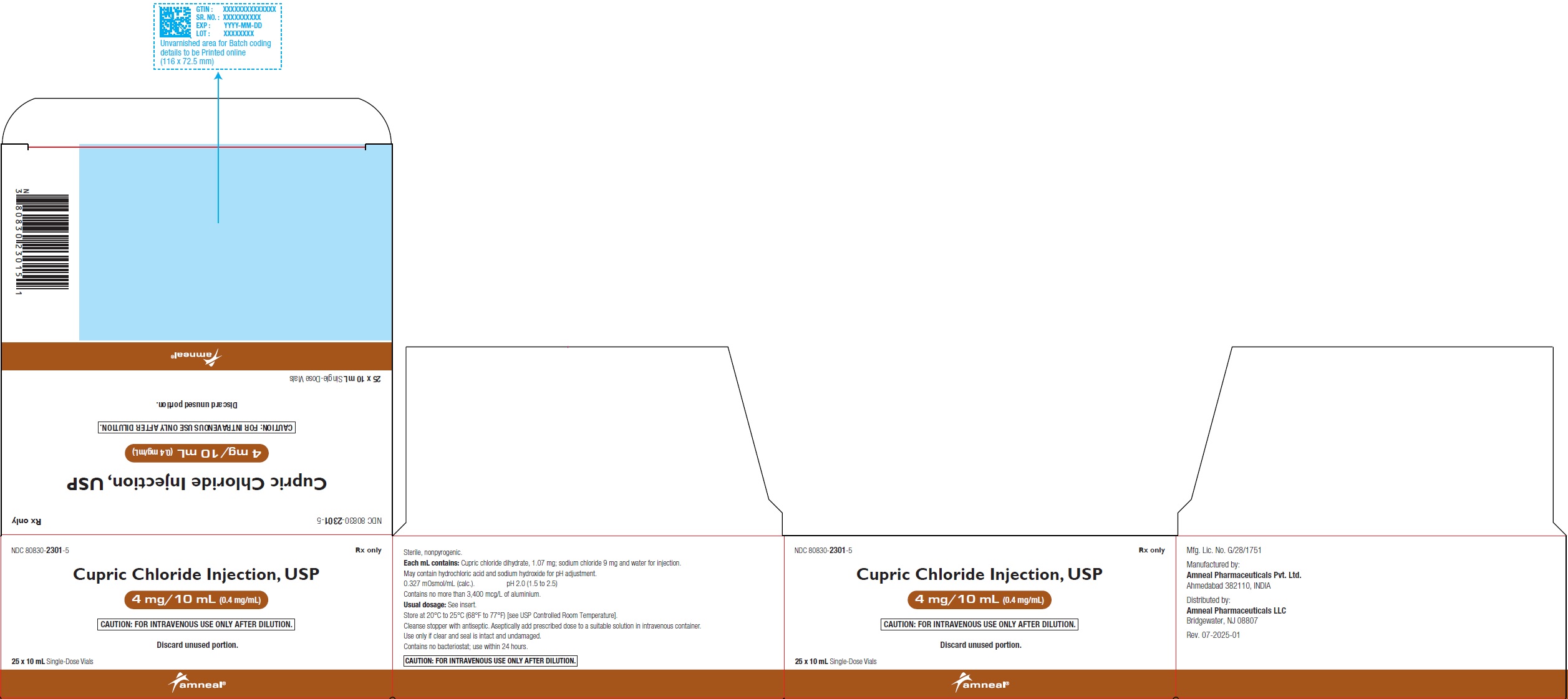 DRUG LABEL: CUPRIC CHLORIDE
NDC: 80830-2301 | Form: INJECTION, SOLUTION
Manufacturer: Amneal Pharmaceuticals Private Limited
Category: prescription | Type: HUMAN PRESCRIPTION DRUG LABEL
Date: 20260204

ACTIVE INGREDIENTS: CUPRIC CHLORIDE 0.4 mg/1 mL
INACTIVE INGREDIENTS: SODIUM CHLORIDE 9 mg/1 mL; HYDROCHLORIC ACID; SODIUM HYDROXIDE; WATER

Cupric Chloride Injection, USP
0.4 mg/mL
FOR INTRAVENOUS USE ONLY AFTER DILUTION
Plastic Vial
Rx only

DESCRIPTION

Cupric chloride injection USP, 0.4 mg/mL is a sterile, clear, colorless to light blue color, nonpyrogenic solution intended for use as an additive to intravenous solutions for total parenteral nutrition (TPN). Each mL of solution contains 1.07 mg cupric chloride dihydrate; 9 mg sodium chloride and water for injection.

The solution contains no bacteriostat, antimicrobial agent or added buffer. The pH is 2.0 (1.5 to 2.5); product may contain hydrochloric acid and sodium hydroxide for pH adjustment. The osmolarity is 0.327 mOsmol/mL (calc.).

Cupric chloride, USP is chemically designated cupric chloride, dihydrate. Its molecular weight is 170.48 g/mol.

The molecular formula is CuCl2 • 2H2O and the structural formula is:

Cupric chloride, USP is a blue to blue-green crystalline compound freely soluble in water, soluble in alcohol and slightly soluble in ether.

Sodium chloride, USP is chemically designated NaCl, a white crystalline compound freely soluble in water.

The semi-rigid vial is fabricated from a specially formulated polyolefin. It is a copolymer of ethylene and propylene. The small amount of water vapor that can pass through the plastic container wall will not significantly alter the drug concentration.

CLINICAL PHARMACOLOGY

Copper is an essential nutrient which serves as a cofactor for serum ceruloplasmin, an oxidase necessary for proper formation of the iron carrier protein, transferrin. Copper also helps maintain normal rates of red and white blood cell formation.

Providing copper during TPN helps prevent development of the following deficiency symptoms: Leukopenia, neutropenia, anemia, depressed ceruloplasmin levels, impaired transferrin formation, secondary iron deficiency and osteoporosis.

Normal serum copper values range from 80 mcg/dl to 163 mcg/dl (mean, approximately 110 mcg/dl). The serum copper level at which deficiency symptoms appear is not precisely defined. In the plasma, about 7% of copper is bound to albumin and amino acids. In the liver, about 93% of copper is bound to ceruloplasmin and released to the serum. The daily turnover of copper through ceruloplasmin is approximately 0.5 mg. Copper is primarily excreted through the bile and into the gastrointestinal tract where it is not reabsorbed. Copper is also eliminated through the kidneys.

INDICATIONS AND USAGE

Cupric chloride injection is indicated for use as a supplement to intravenous solutions given for TPN. Administration helps to maintain copper serum levels and to prevent depletion of endogenous stores and subsequent deficiency symptoms.

CONTRAINDICATIONS

Cupric chloride injection is contraindicated in patients with hypersensitivity to copper (see WARNINGS: Hypersensitivity Reactions).

WARNINGS

Hepatic Accumulation

Copper is primarily eliminated in the bile and excretion is decreased in patients with cholestasis and/or cirrhosis. Hepatic accumulation of copper has been reported in autopsies of patients receiving long-term parenteral nutrition containing copper at dosages higher than recommended.

Administration of copper to patients with cholestasis and/or cirrhosis may cause hepatic accumulation of copper. Administration of copper to patients with Wilson disease, an inborn error of copper metabolism with a defect in hepatocellular copper transport, may cause both increased hepatic accumulation of copper and aggravation of the underlying hepatocellular degeneration.

For patients with cholestasis, biliary dysfunction, or cirrhosis, monitor hepatic and biliary function during long-term administration of cupric chloride injection. If a patient develops signs or symptoms of hepatobiliary disease during the use of cupric chloride injection, obtain serum concentrations of copper and ceruloplasmin and adjust the dose as indicated (see PRECAUTIONS: Hepatic Impairment).

Hypersensitivity Reactions

Post-market safety reporting has identified copper hypersensitivity in women receiving copper-containing intrauterine devices, providing evidence that patients may experience hypersensitivity reactions when exposed to this metal. If hypersensitivity reactions (e.g., pruritis, angioedema, dyspnea, rash, urticaria) occur in patients receiving Cupric Chloride Injection in parenteral nutrition, discontinue the product and initiate appropriate medical treatment (see CONTRAINDICATIONS).

Aluminum Toxicity

This product contains aluminum that may be toxic. Aluminum may reach toxic levels with prolonged parenteral administration if kidney function is impaired. Premature neonates are particularly at risk because their kidneys are immature and they require large amounts of calcium and phosphate solutions, which contain aluminum.

Research indicates that patients with impaired kidney function, including premature neonates, who receive parenteral levels of aluminum at greater than 4 to 5 mcg/kg/day accumulate aluminum at levels associated with central nervous system and bone toxicity. Tissue loading may occur at even lower rates of administration.

PRECAUTIONS

Laboratory Tests

Twice monthly serum assays for copper and/or ceruloplasmin are suggested for monitoring copper concentrations in long-term TPN patients. As ceruloplasmin is a cuproenzyme, ceruloplasmin assays may be depressed secondary to copper deficiency.

Carcinogenesis, Mutagenesis and Impairment of Fertility

Long-term animal studies to evaluate the carcinogenic potential of cupric chloride injection have not been performed, nor have studies been done to assess mutagenesis or impairment of fertility.

Nursing Mothers

It is not known whether this drug is excreted in human milk. Because many drugs are excreted in human milk, caution should be exercised when cupric chloride injection, 0.4 mg/mL is administered to a nursing woman.

Pediatric Use

The safety and effectiveness of cupric chloride injection have been established in pediatric patients receiving parenteral nutrition (see DOSAGE AND ADMINISTRATION).

Pregnancy

Animal reproduction studies have not been conducted with cupric chloride. It is also not known whether cupric chloride can cause fetal harm when administered to a pregnant woman or can affect reproductive capacity. Cupric chloride should be given to a pregnant woman only if clearly indicated.

Geriatric Use

An evaluation of current literature revealed no clinical experience identifying differences in response between elderly and younger patients. In general, dose selection for an elderly patient should be cautious, usually starting at the low end of the dosing range, reflecting the greater frequency of decreased hepatic, renal, or cardiac function and of concomitant disease or other drug therapy.

Hepatic Impairment

Copper is primarily excreted in the bile. Excretion is decreased in patients with cholestasis and/or cirrhosis (see CLINICAL PHARMACOLOGY). Hepatic accumulation of copper has been reported with long-term administration of parenteral nutrition at dosages higher than recommended (see WARNINGS: Hepatic Accumulation). For patients with cholestasis or cirrhosis, monitor hepatic and biliary function during long-term administration of cupric chloride injection. If a patient develops signs or symptoms of hepatobiliary disease during use of cupric chloride injection, obtain serum concentrations of copper and ceruloplasmin.

ADVERSE REACTIONS

None known.

DRUG ABUSE AND DEPENDENCE

None known.

OVERDOSAGE

Acute copper toxicity has been reported in patients with oral, intravenous, or subcutaneous administration. Clinical manifestations included metallic taste, nausea, vomiting, diarrhea, abdominal pain, neurological signs, such as encephalopathy and multi-organ failure involving kidney, liver, blood and cardiovascular systems, which may be fatal. Chelating agents, such as D-penicillamine, can be used for treatment of acute toxicity. Long-term administration of parenteral copper above the recommended dosage may result in significant accumulation of copper in the liver, brain and other tissues with possible organ damage (see WARNINGS: Hepatic Accumulation).

DOSAGE AND ADMINISTRATION

- Cupric chloride injection contains 0.4 mg of copper/mL and is administered intravenously only after dilution. The additive should be diluted in a volume of fluid not less than 100 mL.
- For the adult receiving TPN, the suggested additive dosage of copper is 0.3 mg/day to 0.5 mg/day.
- For pediatric patients, the suggested additive dosage of copper is 20 mcg/kg/day (0.05 mL/kg/day) up to a maximum of 500 mcg/day.
- This product is not appropriate for patients weighing less than 4 kg due to the inability to measure the appropriate amount of the product.
- Do not administer cupric chloride injection intramuscularly because the acidic pH of the solution may cause considerable tissue irritation.

Cupric chloride injection should only be used in conjunction with a pharmacy directed admixture program using aseptic technique in a laminar flow environment; it should be used promptly and in a single operation without any repeated penetrations. The solution contains no preservatives; discard the unused portion immediately after the admixture procedure is completed.

Cupric chloride injection should be inspected visually for particulate matter and discoloration prior to administration. Do not use unless the solution is clear and the seal is intact.

Cupric ion may degrade ascorbic acid in TPN solutions. In order to avoid this loss of ascorbate, multivitamin additives should be added to TPN solutions immediately prior to infusion. Alternatively, the multivitamin additive may be added to one container of TPN solution, followed by copper in a subsequent container.

HOW SUPPLIED

Cupric Chloride Injection USP, 0.4 mg/mL is available as sterile, clear, colorless to light blue color solution filled in 10 mL polypropylene vial with gray rubber stopper and orange flip-off seal.

It is supplied as follows:

4 mg/10 mL (0.4 mg/mL)

1 Single-Dose Vial: NDC 80830-2301-1

25 Vials in 1 Carton: NDC 80830-2301-5

Store at 20°C to 25°C (68°F to 77°F) [see USP Controlled Room Temperature].

Manufactured by:

Amneal Pharmaceuticals Pvt. Ltd.

Ahmedabad 382110, INDIA

Distributed by:

Amneal Pharmaceuticals LLC

Bridgewater, NJ 08807

Rev. 10-2025-03

PRINCIPAL DISPLAY PANEL

NDC 80830-2301-1

Cupric Chloride Injection USP, 4 mg/10 mL (0.4 mg/mL)

Vial label

Rx only

Amneal Pharmaceuticals LLC

NDC 80830-2301-5

Cupric Chloride Injection USP, 4 mg/10 mL (0.4 mg/mL)

Carton label

Rx only

Amneal Pharmaceuticals LLC